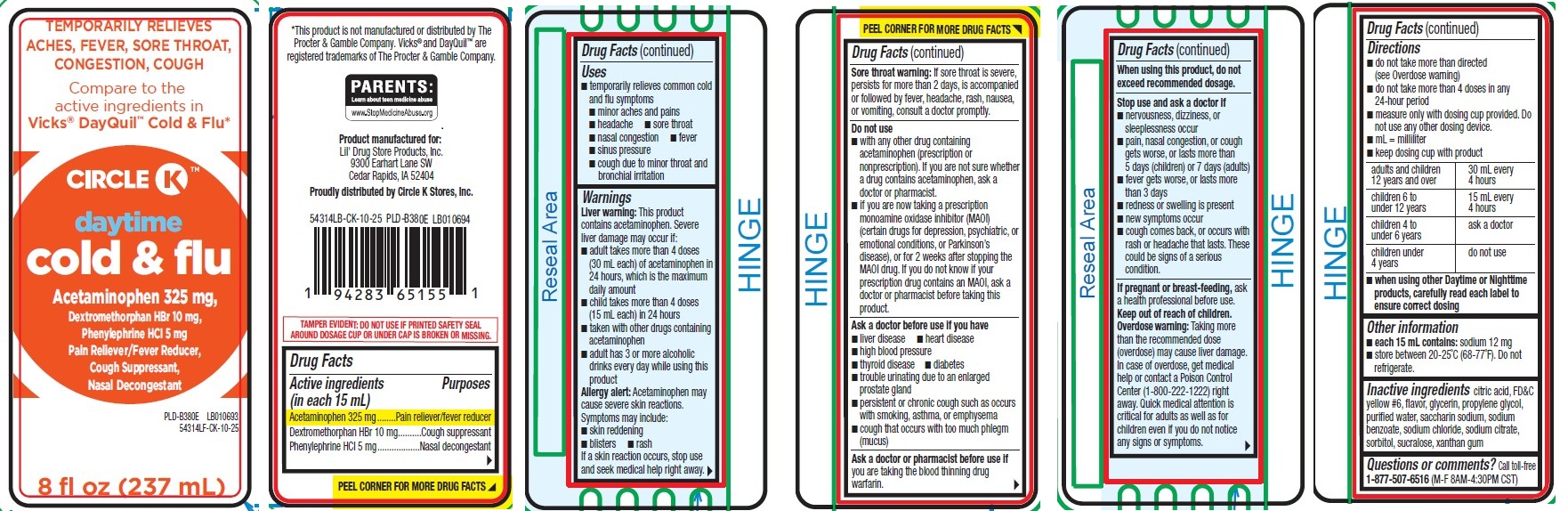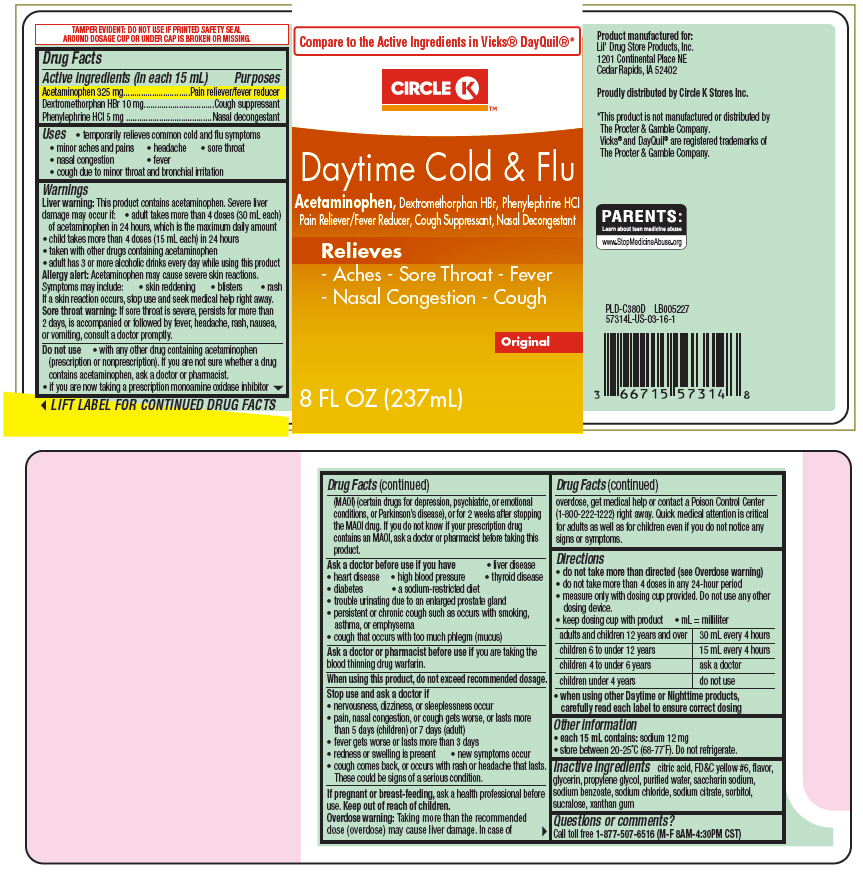 DRUG LABEL: Circle K Daytime Cold and Flu
NDC: 66715-5931 | Form: LIQUID
Manufacturer: Lil' Drug Store Products, Inc.
Category: otc | Type: HUMAN OTC DRUG LABEL
Date: 20251204

ACTIVE INGREDIENTS: ACETAMINOPHEN 325 mg/15 mL; DEXTROMETHORPHAN HYDROBROMIDE 10 mg/15 mL; PHENYLEPHRINE HYDROCHLORIDE 5 mg/15 mL
INACTIVE INGREDIENTS: FD&C YELLOW NO. 6; GLYCERIN; PROPYLENE GLYCOL; WATER; SACCHARIN SODIUM; SODIUM BENZOATE; SODIUM CHLORIDE; TRISODIUM CITRATE DIHYDRATE; SORBITOL; SUCRALOSE; XANTHAN GUM; ANHYDROUS CITRIC ACID

Daytime Cold & Flu, Circle K™

Drug Facts

ACTIVE INGREDIENT

PURPOSE

Active ingredients (in each 15 mL) | Purposes
Acetaminophen 325 mg | Pain reliever/fever reducer
Dextromethorphan HBr 10 mg | Cough suppressant
Phenylephrine HCl 5 mg | Nasal decongestant

Uses

- temporarily relieves common cold and flu symptoms
  - minor aches and pains
  - headache
  - sore throat
  - nasal congestion
  - fever
  - sinus pressure
  - cough due to minor throat and bronchial irritation

Warnings

Liver warning

This product contains acetaminophen. Severe liver damage may occur if:

- adult takes more than 4 doses (30 mL each) of acetaminophen in 24 hours, which is the maximum daily amount
- child takes more than 4 doses (15 mL each) in 24 hours
- taken with other drugs containing acetaminophen
- adult has 3 or more alcoholic drinks every day while using this product

Allergy alert

Acetaminophen may cause severe skin reactions. Symptoms may include:

- skin reddening
- blisters
- rash

If a skin reaction occurs, stop use and seek medical help right away.

Sore throat warning

If sore throat is severe, persists for more than 2 days, is accompanied or followed by fever, headache, rash, nausea, or vomiting, consult a doctor promptly.

Do not use

- with any other drug containing acetaminophen (prescription or nonprescription). If you are not sure whether a drug contains acetaminophen, ask a doctor or pharmacist.
- if you are now taking a prescription monoamine oxidase inhibitor (MAOI) (certain drugs for depression, psychiatric, or emotional conditions, or Parkinson's disease), or for 2 weeks after stopping the MAOI drug. If you do not know if your prescription drug contains an MAOI, ask a doctor or pharmacist before taking this product.

Ask a doctor before use if you have

- liver disease
- heart disease
- high blood pressure
- thyroid disease
- diabetes
- trouble urinating due to an enlarged prostate gland
- persistent or chronic cough such as occurs with smoking, asthma, or emphysema
- cough that occurs with too much phlegm (mucus)

Ask a doctor or pharmacist before use if you are taking the blood thinning drug warfarin.

When using this product, do not exceed recommended dosage.

Stop use and ask a doctor if

- nervousness, dizziness, or sleeplessness occur
- pain, nasal congestion, or cough gets worse, or lasts more than 5 days (children) or 7 days (adult)
- fever gets worse or lasts more than 3 days
- redness or swelling is present
- new symptoms occur
- cough comes back, or occurs with rash or headache that lasts. These could be signs of a serious condition.

PREGNANCY OR BREAST FEEDING

If pregnant or breast-feeding, ask a health professional before use.

Keep out of reach of children.

Overdose warning

Taking more than the recommended dose (overdose) may cause liver damage. In case of overdose, get medical help or contact a Poison Control Center (1-800-222-1222) right away. Quick medical attention is critical for adults as well as for children even if you do not notice any signs or symptoms.

Directions

- do not take more than directed (see Overdose warning)
- do not take more than 4 doses in any 24-hour period
- measure only with dosing cup provided. Do not use any other dosing device.
- keep dosing cup with product
- mL = milliliter

adults and children 12 years and over | 30 mL every 4 hours
children 6 to under 12 years | 15 mL every 4 hours
children 4 to under 6 years | ask a doctor
children under 4 years | do not use

- when using other Daytime or Nighttime products, carefully read each label to ensure correct dosing

Other information

- each 15 mL contains: sodium 12 mg
- store between 20-25°C (68-77°F). Do not refrigerate.

Inactive ingredients

citric acid, FD&C yellow #6, flavor, glycerin, propylene glycol, purified water, saccharin sodium, sodium benzoate, sodium chloride, sodium citrate, sorbitol, sucralose, xanthan gum

Questions or comments?

Call toll free 1-877-507-6516 (M-F 8AM-4:30PM CST)

Proudly distributed by Circle K Stores Inc.

PRINCIPAL DISPLAY PANEL - 237 mL Bottle Label

Compare to the Active Ingredients in Vicks® DayQuil®*

CIRCLE K™

Daytime Cold & Flu

Acetaminophen, Dextromethorphan HBr, Phenylephrine HCl
Pain Reliever/Fever Reducer, Cough Suppressant, Nasal Decongestant

Relieves
- Aches - Sore Throat - Fever
- Nasal Congestion - Cough

Original

8 FL OZ (237mL)

PDP

TEMPORARILY RELIEVES

ACHES, FEVER, SORE THROAT,

CONGESTION, COUGH
Compare to the

active ingredients
in Vicks® DayQuil™ Cold & Flu*

CIRCLE K™

daytime
cold & flu
Acetaminophen 325 mg,
Dextromethorphan HBr 10 mg,

Phenylephrine HCI 5 mg
Pain Reliever/Fever Reducer,

Cough Suppressant,
Nasal Decongestant

8 fl oz (237 mL)